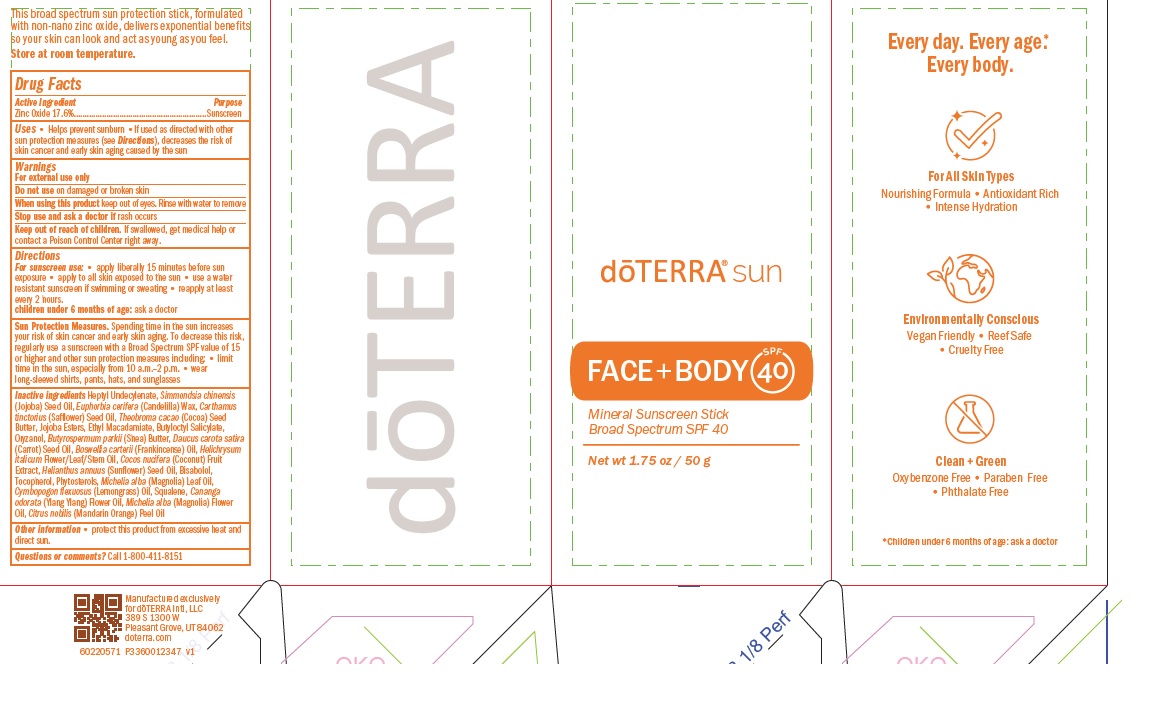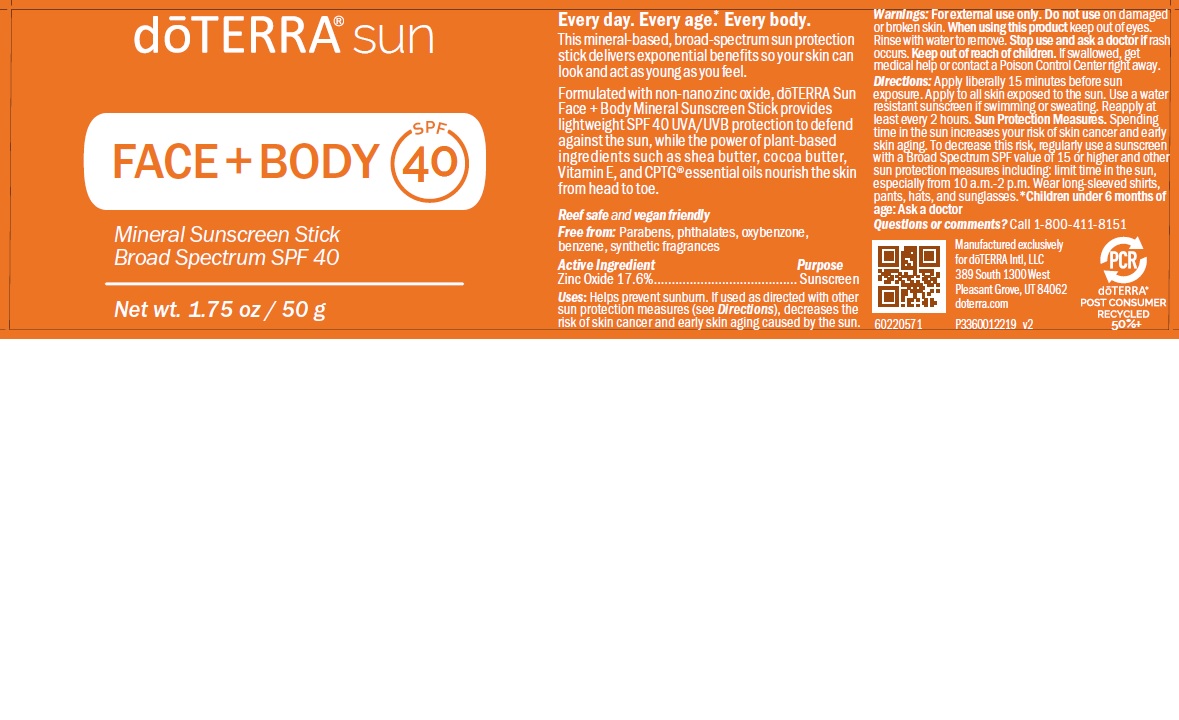 DRUG LABEL: doTERRA Sun
NDC: 71630-175 | Form: STICK
Manufacturer: doTERRA International, LLC
Category: otc | Type: HUMAN OTC DRUG LABEL
Date: 20250205

ACTIVE INGREDIENTS: ZINC OXIDE 17.6 g/100 g
INACTIVE INGREDIENTS: JOJOBA OIL; COCOA BUTTER; HYDROLYZED JOJOBA ESTERS (ACID FORM); ORYZANOL; SHEA BUTTER; SAFFLOWER OIL; ETHYL MACADAMIATE; BUTYLOCTYL SALICYLATE; SUNFLOWER OIL; TOCOPHEROL; MICHELIA ALBA LEAF OIL; EAST INDIAN LEMONGRASS OIL; BUTYLOCTANOL; HEPTYL UNDECYLENATE; CANDELILLA WAX; CITRUS NOBILIS; SQUALENE; WATER; MALIC ACID; HELICHRYSUM ITALICUM FLOWER OIL; CARROT SEED OIL; COCONUT; YLANG-YLANG OIL; FRANKINCENSE OIL

doTERRA Sun Face and Body Mineral Sunscreen Stick

Active Ingredient Purpose
Zinc Oxide 17.6%........................................ Sunscreen

PURPOSE

Sunscreen

INDICATIONS AND USAGE

Uses: Helps prevent sunburn. If used as directed with other
sun protection measures (see Directions), decreases the
risk of skin cancer and early skin aging caused by the sun.

WARNINGS

Warnings: For external use only. Do not use on damaged
or broken skin. When using this product keep out of eyes.
Rinse with water to remove. Stop use and ask a doctor if rash
occurs. Keep out of reach of children. If swallowed, get
medical help or contact a Poison Control Center right away.

WHEN USING

For sunscreen use: • apply liberally 15 minutes before sun
exposure • apply to all skin exposed to the sun • use a water
resistant sunscreen if swimming or sweating • reapply at least
every 2 hours.

Stop use and ask a doctor if rash occurs

Keep out of reach of children. If swallowed, get medical help or
contact a Poison Control Center right away.

Directions

For sunscreen use: • apply liberally 15 minutes before sun
exposure • apply to all skin exposed to the sun • use a water
resistant sunscreen if swimming or sweating • reapply at least
every 2 hours.

Other information • protect this product from excessive heat and
direct sun.

Inactive ingredients Heptyl Undecylenate, Simmondsia chinensis
(Jojoba) Seed Oil, Euphorbia cerifera (Candelilla) Wax, Carthamus
tinctorius (Safflower) Seed Oil, Theobroma cacao (Cocoa) Seed
Butter, Jojoba Esters, Ethyl Macadamiate, Butyloctyl Salicylate,
Oryzanol, Butyrospermum parkii (Shea) Butter, Daucus carota sativa
(Carrot) Seed Oil, Boswellia carterii (Frankincense) Oil, Helichrysum
italicum Flower/Leaf/Stem Oil, Cocos nucifera (Coconut) Fruit
Extract, Helianthus annuus (Sunflower) Seed Oil, Bisabolol,
Tocopherol, Phytosterols, Michelia alba (Magnolia) Leaf Oil,
Cymbopogon flexuosus (Lemongrass) Oil, Squalene, Cananga
odorata (Ylang Ylang) Flower Oil, Michelia alba (Magnolia) Flower
Oil, Citrus nobilis (Mandarin Orange) Peel Oil

doTERRA sun Face + Body Mineral Sunscreen Stick

Mineral sunscreen stick

Broad Spectrum SPF 40